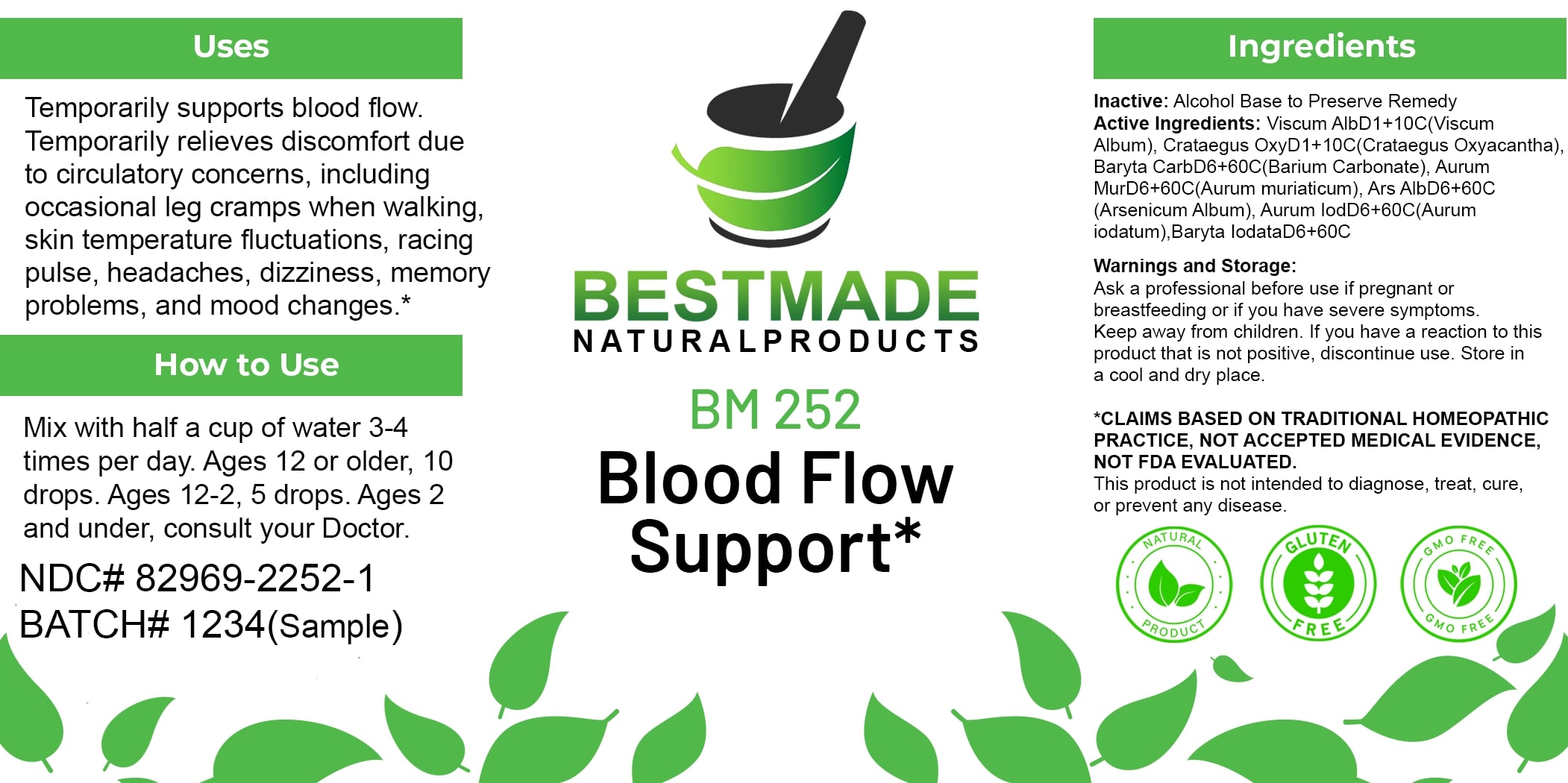 DRUG LABEL: Bestmade Natural Products BM252
NDC: 82969-2252 | Form: LIQUID
Manufacturer: Bestmade Natural Products
Category: homeopathic | Type: HUMAN OTC DRUG LABEL
Date: 20250306

ACTIVE INGREDIENTS: GOLD TRICHLORIDE 30 [hp_C]/30 [hp_C]; GOLD MONOIODIDE 30 [hp_C]/30 [hp_C]; BARIUM IODIDE 30 [hp_C]/30 [hp_C]; VISCUM ALBUM FRUITING TOP 30 [hp_C]/30 [hp_C]; ARSENIC TRIOXIDE 30 [hp_C]/30 [hp_C]; CRATAEGUS LAEVIGATA WHOLE 30 [hp_C]/30 [hp_C]; BARIUM CARBONATE 30 [hp_C]/30 [hp_C]
INACTIVE INGREDIENTS: ALCOHOL 30 [hp_C]/30 [hp_C]

BM252

DOSAGE AND ADMINISTRATION

How to Use

Mix with half a cup of water 3-4 times per day. Ages 12 or older, 10 drops. Ages 12-2, 5 drops. Ages 2 and under, consult your Doctor.

INACTIVE INGREDIENT

Ingredients

Inactive: Alcohol Base to Preserve Remedy

ACTIVE INGREDIENT

Active Ingredients: Viscum Alb D1+10C (Viscum Album), Crataegus Oxy D1+10C (Crataegus Oxyacantha), Baryta Carb D6+60C (Barium Carbonate), Aurum Mur D6+60C (Aurum muriaticum), Ars Alb D6+60C (Arsenicum Album), Aurum Iod D6+60C (Aurum iodatum), Baryta Iodata D6+60C

Uses

Temporarily supports blood flow. Temporarily relieves discomfort due to circulatory concerns, including occasional leg cramps when walking, skin temperature fluctuations, racing pulse, headaches, dizziness, memory problems, and mood changes.*

*CLAIMS BASED ON TRADITIONAL HOMEOPATHIC PRACTICE, NOT ACCEPTED MEDICAL EVIDENCE, NOT FDA EVALUATED.

This product is not intended to diagnose, treat, cure, or prevent any disease.

Uses

Temporarily supports blood flow. Temporarily relieves discomfort due to circulatory concerns, including occasional leg cramps when walking, skin temperature fluctuations, racing pulse, headaches, dizziness, memory problems, and mood changes.*

*CLAIMS BASED ON TRADITIONAL HOMEOPATHIC PRACTICE, NOT ACCEPTED MEDICAL EVIDENCE, NOT FDA EVALUATED.

This product is not intended to diagnose, treat, cure, or prevent any disease.

KEEP OUT OF REACH OF CHILDREN

Warnings and Storage:

Ask a professional before use if pregnant or breastfeeding or if you have severe symptoms. Keep away from children. If you have a reaction to this product that is not positive, discontinue use. Store in a cool and dry place.

Warnings and Storage:

Ask a professional before use if pregnant or breastfeeding or if you have severe symptoms. Keep away from children. If you have a reaction to this product that is not positive, discontinue use. Store in a cool and dry place.

*CLAIMS BASED ON TRADITIONAL HOMEOPATHIC PRACTICE, NOT ACCEPTED MEDICAL EVIDENCE NOT FDA EVALUATED.

This product is not intended to diagnose, treat, cure, or prevent any disease.

Entire package label